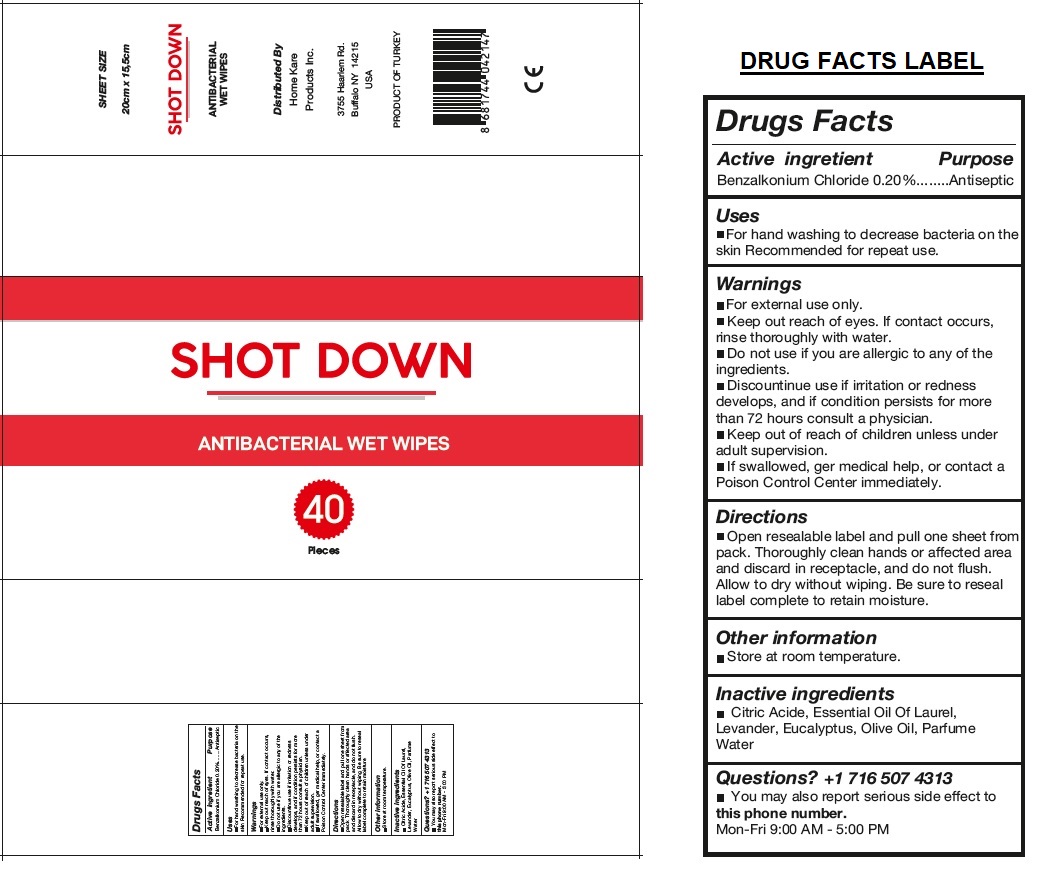 DRUG LABEL: SHOT DOWN
NDC: 81402-101 | Form: CLOTH
Manufacturer: Private Label Aerosol Dolum Sanayi Ticaret Anonim Sirketi
Category: otc | Type: HUMAN OTC DRUG LABEL
Date: 20210115

ACTIVE INGREDIENTS: BENZALKONIUM CHLORIDE 0.20 g/100 mL
INACTIVE INGREDIENTS: CITRIC ACID MONOHYDRATE; BAY LEAF OIL; LAVENDER OIL; EUCALYPTUS OIL; OLIVE OIL; WATER

SHOT DOWN ANTIBACTERIAL WET WIPES

Active ingredient

Benzalkonium Chloride 0.20%

Purpose

Antiseptic

Uses

• For hand washing to decrease bacteria on the skin. Recommended for repeat use.

Warnings

• For external use only.
• Keep out reach of eyes. If contact occurs, rinse thoroughly with water.
• Do not use if you are allergic to any of the ingredients.
• Discontinue use if irritation or redness develops, and if condition persists for more than 72 hours consult a physician.

• Keep out of reach of children unless under adult supervision.
• If swallowed, get medical help, or contact a Poison Control Center immediately.

Directions

• Open resealable label and pull one sheet from pack. Thoroughly clean hands or affected area and discard in receptacle, and do not flush. Allow to dry without wiping. Be sure to reseal label complete to retain moisture.

Other information

• Store at room temperature.

Inactive ingredients

Citric Acid, Essential Oil Of Laurel, Lavender, Eucalyptus, Olive Oil, Parfum, Water

Questions? +1 716 507 4313

• You may also report serious side effect to this phone number.
Mon-Fri 9:00 AM - 5:00 PM

Distributed By
Home Kare Products Inc.

3755 Haarlem Rd.
Buffalo NY 14215
USA

PRODUCT OF TURKEY